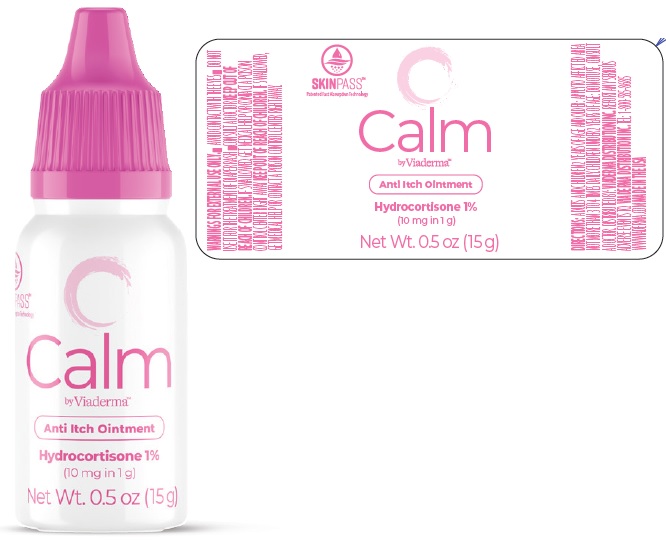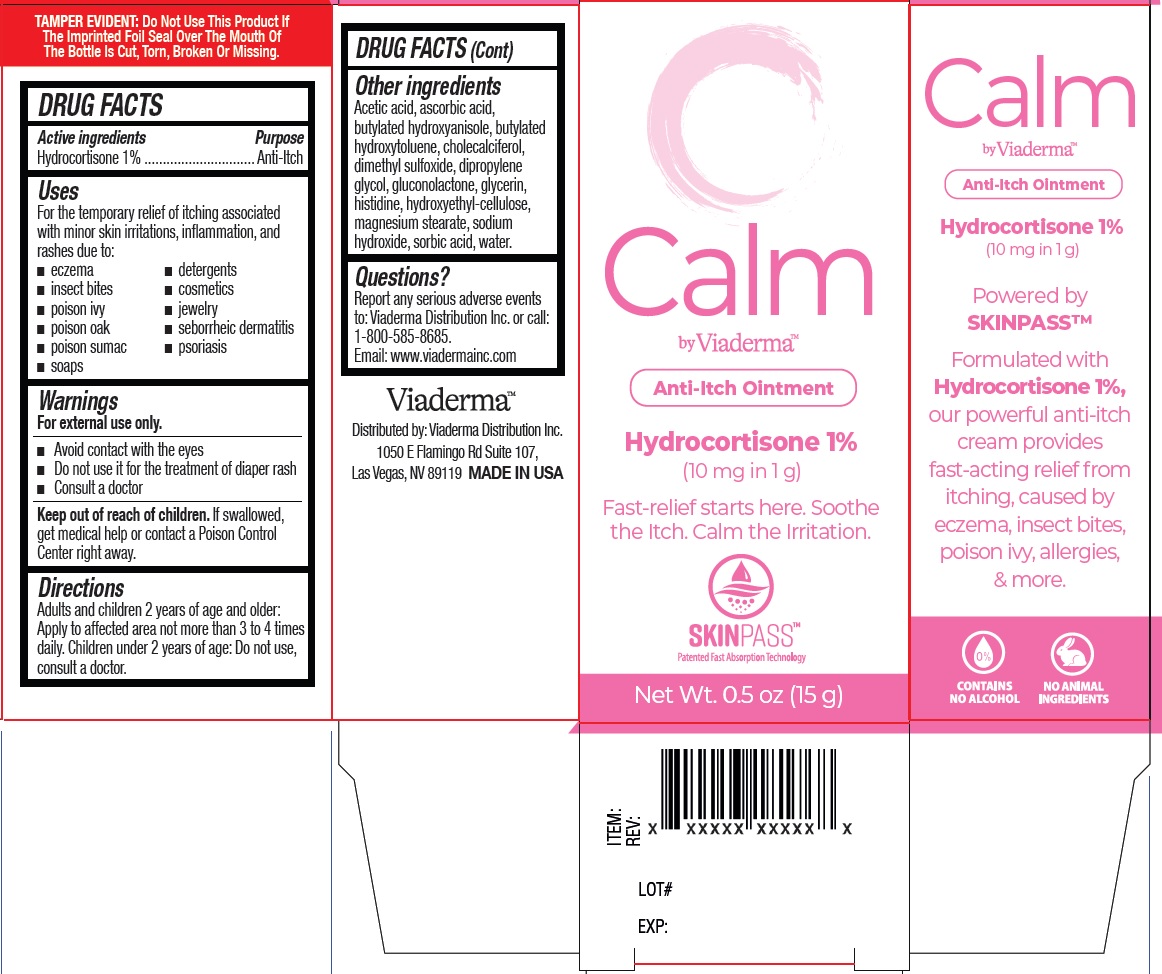 DRUG LABEL: Viaderma Calm Anti-Itch
NDC: 71262-014 | Form: OINTMENT
Manufacturer: ViaDerma Distribution, Inc.
Category: otc | Type: HUMAN OTC DRUG LABEL
Date: 20251001

ACTIVE INGREDIENTS: HYDROCORTISONE 10 mg/1 g
INACTIVE INGREDIENTS: ACETIC ACID; ASCORBIC ACID; BUTYLATED HYDROXYANISOLE; BUTYLATED HYDROXYTOLUENE; CHOLECALCIFEROL; DIMETHYL SULFOXIDE; DIPROPYLENE GLYCOL; GLUCONOLACTONE; GLYCERIN; HISTIDINE; HYDROXYETHYL CELLULOSE, UNSPECIFIED; MAGNESIUM STEARATE; SODIUM HYDROXIDE; SORBIC ACID; WATER

Viaderma Calm Anti-Itch Ointment

Active ingredients

Hydrocortisone 1%

Purposes

Anti-Itch

Uses

For the temporary relief of itching associated with minor skin irritations, inflammation, and rashes due to:
• eczema • detergents
• insect bites • cosmetics
• poison ivy • jewelry
• poison oak • seborrheic dermatitis
• poison sumac • psoriasis
• soaps

Warnings

For external use only.

Avoid contact with the eyes

Do not use

- it for the treatment of diaper rash
- Consult a doctor

Keep out of reach of children.

If swallowed, get medical help or contact a Poison Control Center right away.

Directions

Adults and children 2 years of age and older: Apply to affected area not more than 3 to 4 times daily. Children under 2 years of age: Do not use, consult a doctor.

Other ingredients

Acetic acid, ascorbic acid, butylated hydroxyanisole, butylated hydroxytoluene, cholecalciferol, dimethyl sulfoxide, dipropylene glycol, gluconolactone, glycerin, histidine, hydroxyethyl-cellulose, magnesium stearate, sodium hydroxide, sorbic acid, water.

Questions?

Report any serious adverse events
to: Viaderma Distribution Inc. or call:
1-800-585-8685.
Email: www.viadermainc.com